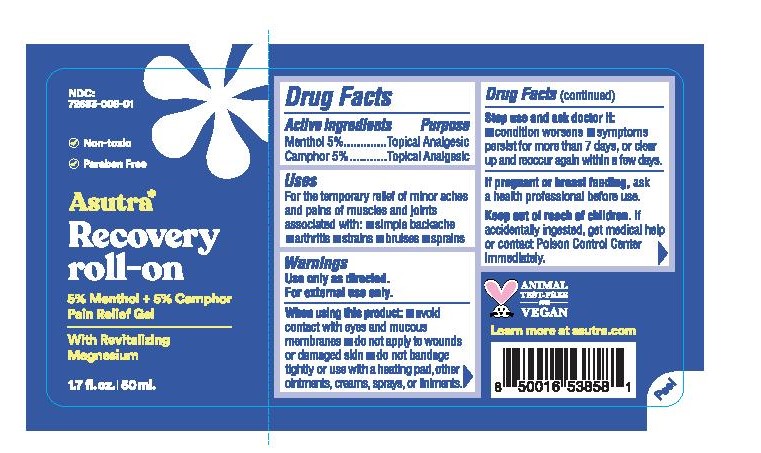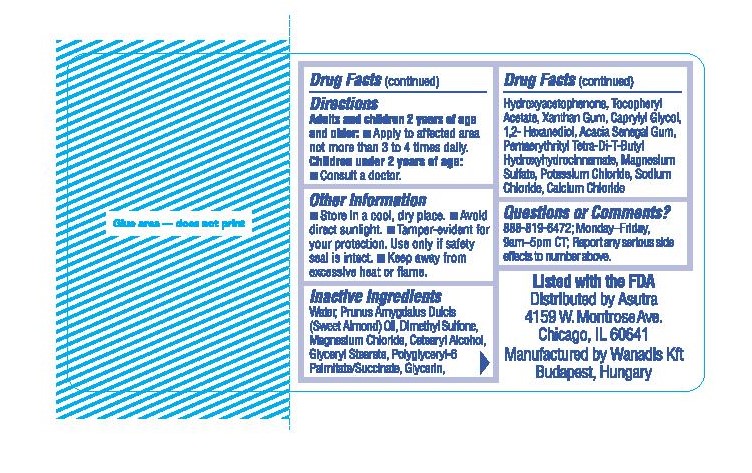 DRUG LABEL: Recovery Roll-On
NDC: 72683-008 | Form: GEL
Manufacturer: PROXIMITY CAPITAL PARTNERS LLC DBA ASUTRA
Category: otc | Type: HUMAN OTC DRUG LABEL
Date: 20250618

ACTIVE INGREDIENTS: CAMPHOR (NATURAL) 5 g/100 mL; MENTHOL 5 g/100 mL
INACTIVE INGREDIENTS: POLYGLYCERYL-6 STEARATE; .ALPHA.-TOCOPHEROL ACETATE, D-; 1,2-HEXANEDIOL; ALMOND OIL; ACACIA; PENTAERYTHRITOL TETRAKIS(3-(3,5-DI-TERT-BUTYL-4-HYDROXYPHENYL)PROPIONATE); POTASSIUM CHLORIDE; SODIUM CHLORIDE; CALCIUM CHLORIDE; CAPRYLYL GLYCOL; MAGNESIUM SULFATE, UNSPECIFIED FORM; GLYCERIN; DIMETHYL SULFONE; CETOSTEARYL ALCOHOL; WATER; MAGNESIUM CHLORIDE; GLYCERYL STEARATE SE; HYDROXYACETOPHENONE; XANTHAN GUM

Recovery Roll-On (Asutra)

Active Ingredients

Menthol 5%

Camphor 5%

Purpose

Menthol 5%.............Topical Analgesic

Camphor 5%.............Topical Analgesic

Uses

For the temporary relief of minor aches and pains of muscles and joints associated with:

- simple backache
- arthritis
- strains
- bruises
- sprains

Warnings

Use only as directed.

For external use only.

When using this product:

- avoid contact with eyes and mucous membranes
- do not apply to wounds or damaged skin
- do not bandage tightly or use with a heating pad, other ointments, creams, sprays, or liniments.

Stop use and ask doctor if:

- condition worsens
- symptoms persist for more than 7 days, or clear up and reoccur again within a few days.

PREGNANCY OR BREAST FEEDING

If pregnant or breastfeeding,ask a health professional before use.

Keep out of reach of children.If accidentally ingested, get medical help or contact Poison Control Center immediately.

Directions

Adults and children 2 years of age and older:

- Apply to affected area not more than 3 to 4 times daily.

Children under 2 years of age:

- Consult a doctor.

Other Information

- Store in a cool, dry place.
- Avoid direct sunlight.
- Tamper-evident for your protection. Use only if safety seal is intact.
- Keep away from excessive heat or flame.

Inactive Ingredients

Water, Prunus Amygdalus Dulcis (Sweet Almond) Oil, Dimethyl Sulfone, Magnesium Chloride, Cetearyl Alcohol, Glyceryl Stearate, Polyglyceryl-6 Palmitate/Succinate, Glycerin, Hydroxyacetophenone, Tocopheryl Acetate, Xanthan Gum, Caprylyl Glycol, 1,2-Hexanediol, Acacia Senegal Gum, Pentaerythrityl Tetra-Di-T-Butyl Hydroxyhydrocinnamate, Magnesium Sulfate, Potassium Chloride, Sodium Chloride, Calcium Chloride

Questions or Comments?

888-819-6472; Monday-Friday, 9am-5pm CT; Report any serious side effects to number above.

PACKAGE LABEL

NDC: 72683-008-01

Non-toxic

Paraben Free

Asutra*

Recovery Roll-On

5% Menthol + 5% Camphor

Pain Relief Gel

With Revitalizing Magnesium

1.7 fl. oz. | 50 ml.